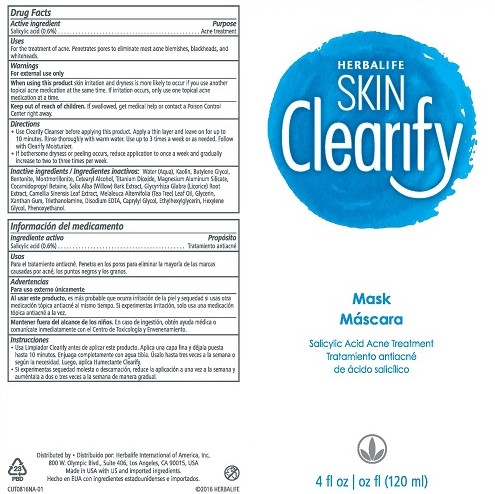 DRUG LABEL: Skin Clearify Mask
NDC: 51785-816 | Form: LIQUID
Manufacturer: Herbalife International of America Inc.
Category: otc | Type: HUMAN OTC DRUG LABEL
Date: 20161010

ACTIVE INGREDIENTS: SALICYLIC ACID 0.6 g/100 mL
INACTIVE INGREDIENTS: TITANIUM DIOXIDE; SALIX ALBA BARK; KAOLIN; BENTONITE; GLYCYRRHIZA GLABRA; GREEN TEA LEAF; TEA TREE OIL; GLYCERIN; PHENOXYETHANOL; WATER; BUTYLENE GLYCOL; ETHYLHEXYLGLYCERIN; XANTHAN GUM; EDETATE DISODIUM; TROLAMINE; CAPRYLYL GLYCOL; HEXYLENE GLYCOL; MONTMORILLONITE; CETOSTEARYL ALCOHOL; MAGNESIUM ALUMINUM SILICATE; COCAMIDOPROPYL BETAINE

Clearify Acne Mask

Drug Facts

Active ingredient

Salicylic acid (0.6%)

Purpose

Acne treatment

Uses

For the treatment of acne. Penetrates pores to eliminate most acne blemishes, blackheads, and whiteheads.

Warnings

For external use only

When using this product skin irritation and dryness is more likely to occur if you use another topical acne medication at the same time. If irritation occurs, only use one topical acne medication at a time.

Keep out of reach of children. If swallowed, get medical help or contact a Poison Control Center right away.

Directions

- Use Clearify Cleanser before applying this product. Apply a thin layer and leave on for up to 10 minutes. Rinse thoroughly with warm water. Use up to 3 times a week or as needed. Follow with Clearify Moisturizer.
- If bothersome dryness or peeling occurs, reduce application to once a week and gradually increase to two to three times per week.

INACTIVE INGREDIENT

Inactive ingredients: Water (Aqua), Kaolin, Butylene Glycol, Bentonite, Montmorillonite, Cetearyl Alcohol, Titanium Dioxide, Magnesium Aluminum Silicate, Cocamidopropyl Betaine, Salix Alba (Willow) Bark Extract, Glycyrrhiza Glabra (Licorice) Root Extract, Camellia Sinensis Leaf Extract, Melaleuca Alternifolia (Tea Tree) Leaf Oil, Glycerin, Xanthan Gum, Triethanolamine, Disodium EDTA, Caprylyl Glycol, Ethylhexylglycerin, Hexylene Glycol, Phenoxyethanol.

Distributed by: Herbalife International of America, Inc.

800 W. Olympic Blvd., Suite 406, Los Angeles, CA 90015 USA

Made in USA with US and imported ingredients.

© 2016 HERBALIFE

PACKAGE LABEL

HERBALIFE

SKIN Clearify

Mask

Salicylic Acid Acne Treatment

4 fl oz (120 ml)